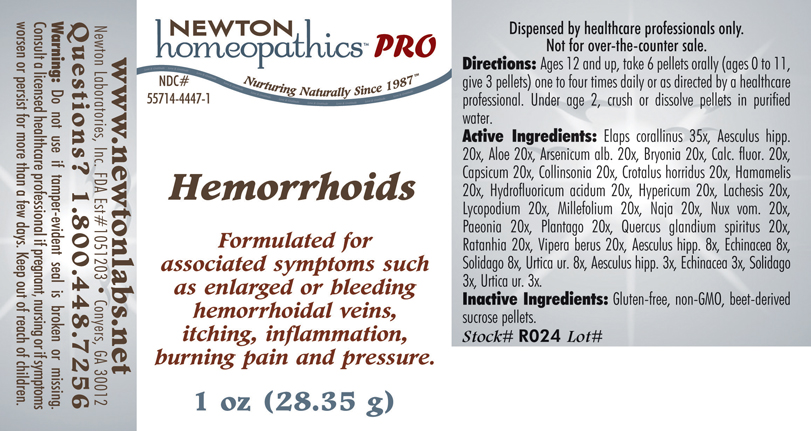 DRUG LABEL: Hemorrhoids 
NDC: 55714-4447 | Form: PELLET
Manufacturer: Newton Laboratories, Inc.
Category: homeopathic | Type: HUMAN PRESCRIPTION DRUG LABEL
Date: 20110601

ACTIVE INGREDIENTS: Micrurus Corallinus Venom 35 [hp_X]/1 g; Horse Chestnut 20 [hp_X]/1 g; Aloe 20 [hp_X]/1 g; Arsenic Trioxide 20 [hp_X]/1 g; Bryonia Alba Root 20 [hp_X]/1 g; Calcium Fluoride 20 [hp_X]/1 g; Capsicum 20 [hp_X]/1 g; Collinsonia Canadensis Root 20 [hp_X]/1 g; Crotalus Horridus Horridus Venom 20 [hp_X]/1 g; Hamamelis Virginiana Root Bark/stem Bark 20 [hp_X]/1 g; Hydrofluoric Acid 20 [hp_X]/1 g; Hypericum Perforatum 20 [hp_X]/1 g; Lachesis Muta Venom 20 [hp_X]/1 g; Lycopodium Clavatum Spore 20 [hp_X]/1 g; Achillea Millefolium 20 [hp_X]/1 g; Naja Naja Venom 20 [hp_X]/1 g; Strychnos Nux-vomica Seed 20 [hp_X]/1 g; Paeonia Officinalis Root 20 [hp_X]/1 g; Plantago Major 20 [hp_X]/1 g; Quercus Robur Nut 20 [hp_X]/1 g; Krameria Lappacea Root 20 [hp_X]/1 g; Vipera Berus Venom 20 [hp_X]/1 g; Echinacea, Unspecified 8 [hp_X]/1 g; Solidago Virgaurea Flowering Top 8 [hp_X]/1 g; Urtica Urens 8 [hp_X]/1 g
INACTIVE INGREDIENTS: Sucrose

Hemorrhoids

INDICATIONS & USAGE SECTION

HEMORRHOIDS Formulated for associated symptoms such as enlarged or bleeding hemorrhoidal veins, itching, inflammation, burning pain and pressure.

DOSAGE & ADMINISTRATION SECTION

Directions: Ages 12 and up, take 6 pellets orally (ages 0 to 11, give 3 pellets) one to four times daily or as directed by a healthcare professional. Under age 2, crush or dissolve pelles in purified water.

ACTIVE INGREDIENT SECTION

Elaps corallinus 35x, Aesculus hipp. 20x, Aloe 20x, Arsenicum alb. 20x, Bryonia 20x, Calc. fluor. 20x, Capsicum 20x, Collinsonia 20x, Crotalus horridus 20x, Hamamelis 20x, Hydrofluoricum acidum 20x, Hypericum 20x, Lachesis 20x, Lycopodium 20x, Millefolium 20x, Naja 20x, Nux vom. 20x, Paeonia 20x, Plantago 20x, Quercus glandium spiritus 20x, Ratanhia 20x, Vipera berus 20x, Aesculus hipp 8x, Echinacea 8x, Solidago 8x, Urtica ur. 8x, Aesculus hipp. 3x, Echinacea 3x, Solidago 3x, Urtica ur. 3x.

PURPOSE SECTION

Formulated for associated symptoms such as enlarged or bleeding hemorrhoidal veins, itching, inflammation, burning pain and pressure.

INACTIVE INGREDIENT SECTION

Inactive Ingredients: Gluten-free, non-GMO, beet-derived sucrose pellets.

QUESTIONS SECTION

www.newtonlabs.net Newton Laboratories, Inc. FDA Est # 1051203 - Conyers, GA 30012
Questions? 1.800.448.7256

WARNINGS? SECTION

Warning: Do not use if tamper - evident seal is broken or missing. Consult a licensed healthcare professional if pregnant, nursing or if symptoms worsen or persist for more than a few days. Keep out of reach of children.

PREGNANCY OR BREAST FEEDING SECTION

Consult a licensed healthcare professional if pregnant or nursing or if symptoms worsen or persist for more than a few days.

KEEP OUT OF REACH OF CHILDREN SECTION

Keep out of reach of children.